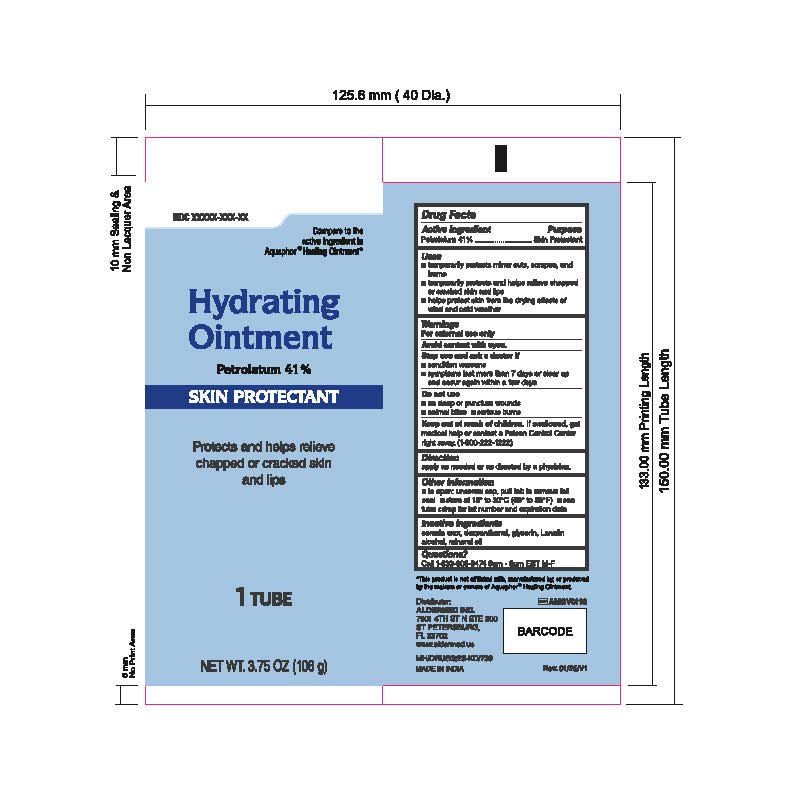 DRUG LABEL: Hydrating
NDC: 87236-010 | Form: CREAM
Manufacturer: Aldermed Inc.
Category: otc | Type: HUMAN OTC DRUG LABEL
Date: 20260212

ACTIVE INGREDIENTS: PETROLATUM 41 g/100 g
INACTIVE INGREDIENTS: CERESIN; DEXPANTHENOL; GLYCERIN; LANOLIN ALCOHOLS; MINERAL OIL

Hydrating Ointment

Active ingredient

Petrolatum 41%

Purpose

Skin Protectant

Uses

■ temporarily protects minor cuts, scrapes, and burns

■ temporarily protects and helps relieve chapped or cracked skin and lips
■ helps protect skin from the drying effects of wind and cold weather

Warnings

For External Use Only

Avoid contact with eyes

Stop use and ask a doctor if

- Conditions worsens
- Symptoms last more than 7 days or clear up and occur again within a few days

Do not use

• On deep puncture wounds • Animal bites • Serious burns.

Keep out of reach of children

If swallowed, get medical help or contact a Poison Control Center right away (1-800-222-1222).

Directions

Apply as needed or as directed by a physician

Other information

■ to open: unscrew cap, pull tab to remove foil seal

■ store at 15° to 30°C (59° to 86°F)

■ see tube crimp for lot number and expiration date

Inactive Ingredients

ceresin wax, dexpanthenol, glycerin, Lanolin alcohol, mineral oil

Questions?

Call 1-833-605-84-74 9am-5 pm EST M-F